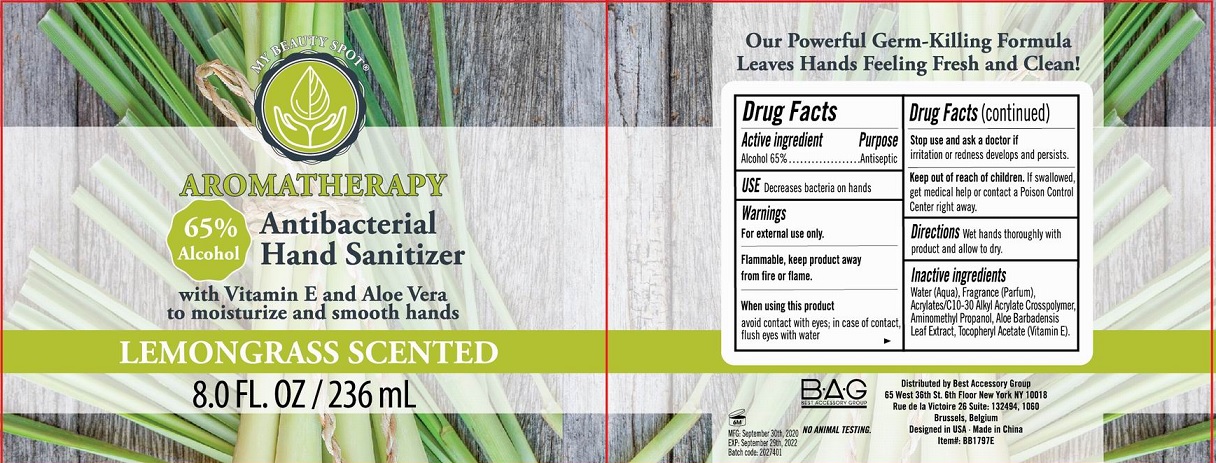 DRUG LABEL: Aromatherapy Antibacterial Hand Sanitizer Lemongrass Scented
NDC: 56136-475 | Form: GEL
Manufacturer: Ganzhou Olivee Cosmetic Co., Ltd.
Category: otc | Type: HUMAN OTC DRUG LABEL
Date: 20201112

ACTIVE INGREDIENTS: ALCOHOL 65 mL/100 mL
INACTIVE INGREDIENTS: WATER; CARBOMER COPOLYMER TYPE A; AMINOMETHYLPROPANOL; .ALPHA.-TOCOPHEROL ACETATE, DL-; ALOE VERA LEAF

HAND SANITIZER

Active ingredient

Alcohol 65%

Purpose

Antiseptic

Use

Decreases bacteria on hands

Warnings

For external use only.

Flammable. Keep product away from fire or flame.

When using this product avoid contact with eyes. In case of contact flush eyes with water.

Stop use and ask a doctor if irritation orredness develops and persists.

Keep out of reach of children.

If swallowed, get medical help or contact a Poison Control Center right away.

Directions

Wet hands thoroughly with product and allow to dry.

Inactive ingredients

Water (Aqua), Acrylates/C10-30 Alkyl Acrylate Crosspolymer, Aminomethyl Propanol, Fragrance (Parfum), Aloe Barbadensis leaf Extract, Tocopheryl Acetate (Vitamin E).